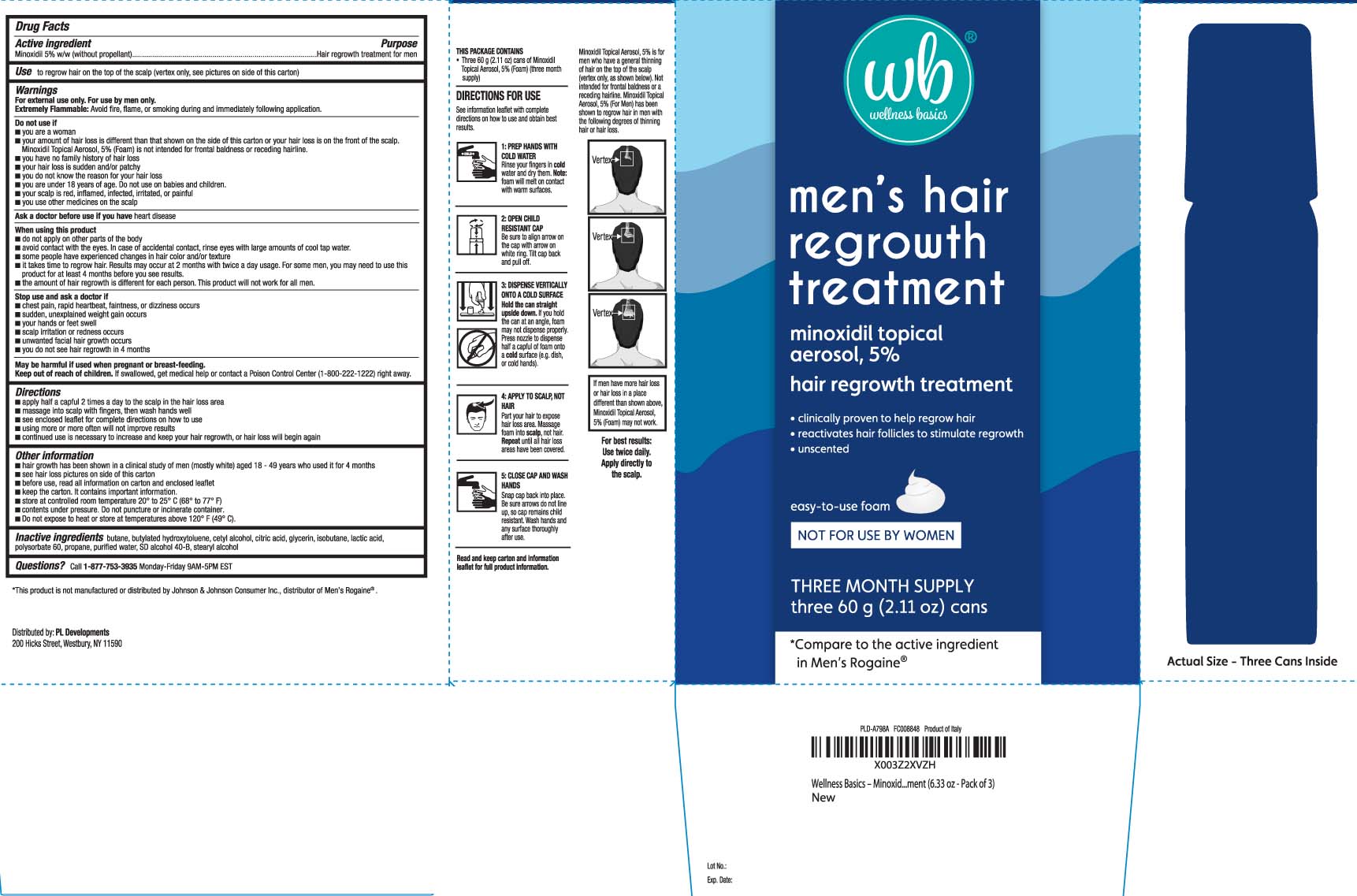 DRUG LABEL: Minoxidil
NDC: 59726-125 | Form: AEROSOL, FOAM
Manufacturer: P & L Development, LLC
Category: otc | Type: HUMAN OTC DRUG LABEL
Date: 20241105

ACTIVE INGREDIENTS: MINOXIDIL 50 mg/1 mL
INACTIVE INGREDIENTS: BUTANE; BUTYLATED HYDROXYTOLUENE; CETYL ALCOHOL; CITRIC ACID MONOHYDRATE; GLYCERIN; ISOBUTANE; LACTIC ACID; POLYSORBATE 60; PROPANE; WATER; ALCOHOL; STEARYL ALCOHOL

Minoxidil Topical Solution for Men

Active ingredient

Minoxidil, USP 5% w/v (without propellant)

Purpose

Hair regrowth treatment for men

Use

to regrow hair on the top of the scalp (vertex only, see pictures on side of carton)

Warnings

For external use only. For use by men only.
Flammable: Avoid fire. flame, or smoking during and immediately following application

Do not use if

- you are a woman
- your amount of hair loss is different than that shown on the side of this carton or your hair loss is on the front of the scalp. Minoxidil topical Aerosol, 5% (Foam) is not intended for frontal baldness or receding hairline.
- you have no family history of hair loss
- your hair loss is sudden and/or patchy
- you do not know the reason for your hair loss
- you are under 18 years of age. Do not use on babies and children.
- your scalp is red, inflamed, infected, irritated, or painful
- you use other medicines on the scalp

Ask a doctor before use if you have

heart disease

When using this product

- do not apply on other parts of the body
- avoid contact with the eyes. In case of accidental contact, rinse eyes with large amounts of cool tap water.
- some people have experienced changes in hair color and/or texture
- it takes time to regrow hair. Results may occur at 2 months with twice a day usage. For some men, you may need to use this product for at least 4 months before you see results.
- the amount of hair regrowth is different for each person. This product will not work for all men.

Stop use and ask a doctor if

- chest pain, rapid heartbeat, faintness, or dizziness occurs
- sudden, unexplained weight gain occurs
- your hands or feet swell
- scalp irritation or redness occurs
- unwanted facial hair growth occurs
- you do not see hair regrowth in 4 months

Keep out of reach of children.

If swallowed, get medical help or contact a Poison Control Center (1-800-222-1222) right away.

Directions

- apply half a capful 2 times a day to the scalp in the hair loss area
- massage into scalp with fingers, then wash hands well
- see enclosed leaflet for complete directions on how to use
- using more or more often will not improve results
- continued use is necessary to increase and keep your hair regrowth, or hair loss will begin again

Other information

- hair growth has been shown in clinical study of men (mostly white) aged 18-49 years who used it for 4 month
- see hair loss pictures on side of this carton
- before use, read all information on carton and enclosed leaflet
- keep the carton. It contains important information.
- store at controlled room temperature 20° to 25°C (68° to 77°F)
- contents under pressure. Do not puncture or incinerate container.
- Do not expose to heat or store at temperatures above 120º F (49º C).

Inactive ingredients

butane, butylated hydroxytoluene, cetyl alcohol, citric acid glycerin, isobutane, lactic acid, polysorbate 60, propane, purified water, SD alcohol 40-B, stearyl alcohol

Questions?

Call 1-877-753-3935 Monday-Friday 9AM-5PM EST

Principal display panel

*Compare to the active ingredient in Men's Rogaine®

men's hair regrowth treatment

Minoxidil Topical aerosol, 5%

hair regrowth treatment

- Clinically proven to help regrow hair
- reactivates hair follicles to stimulate regrowth
- unscented

easy-to-use foam

NOT FOR USE BY WOMEN

THREE MONTH SUPPLY

THREE 60 G (2.11 OZ) CANS

mL (FL OZ) BOTTLE

*This product is not manufactured by, or distributed by Johnson & Johnson Comsumer Inc., distributor of Men's Rogaine®

Distributed by: PL Developments

200 Hicks Street, Westbury, NY 11590

Package label

WELLNESS BASICS Men's Hair regrowth Treatment